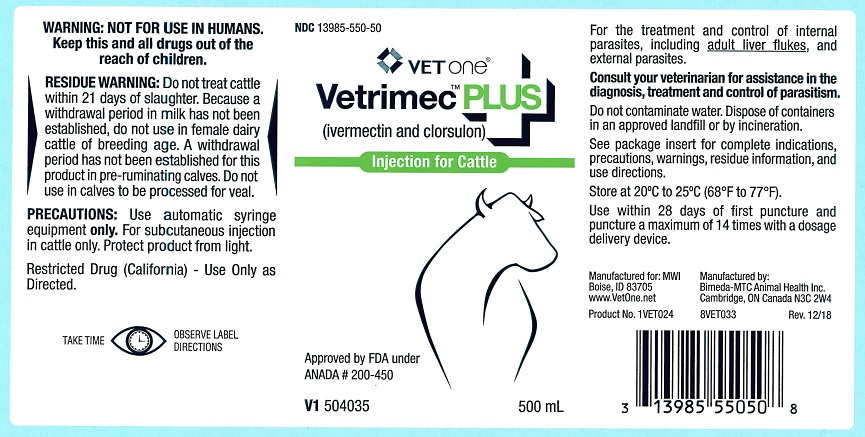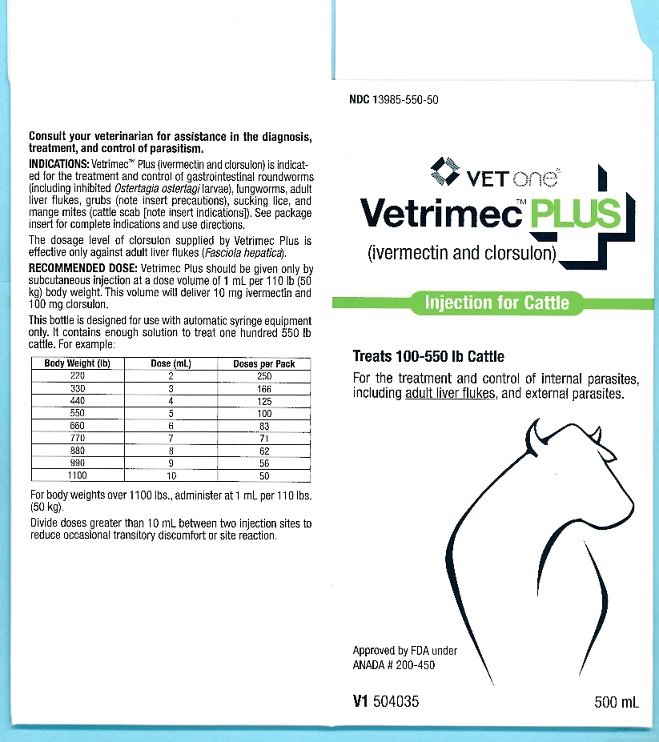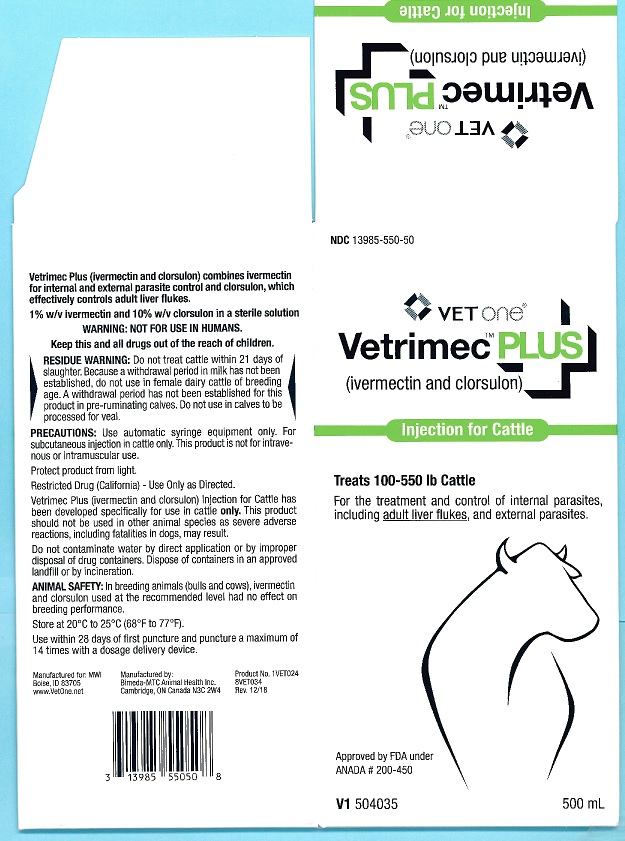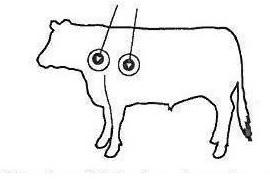 DRUG LABEL: Vetrimec Plus
NDC: 13985-550 | Form: INJECTION
Manufacturer: VetOne
Category: animal | Type: OTC ANIMAL DRUG LABEL
Date: 20241211

ACTIVE INGREDIENTS: IVERMECTIN 10 mg/1 mL; CLORSULON 100 mg/1 mL

DESCRIPTION

Approved by FDA under ANADA #200-450

Restricted Drug (California)-Use Only as Directed

Vetrimec™ Plus

(ivermectin and clorsulon)

Injection for Cattle

For the effective treatment and control of internal parasites, including adult liver flukes, and external parasites.

Consult your veterinarian for assistance in the diagnosis, treatment and control of parasitism.

INTRODUCTION: The ability of ivermectin to deliver internal and external parasite control has been proven in cattle markets around the world. Now, Vetrimec™ Plus combines ivermectin, the active ingredient of Vetrimec™ 1%, with clorsulon, an effective adult flukicide. A single injection of Vetrimec™ Plus (ivermectin and clorsulon) offers all the benefts of Vetrimec™ 1% plus control of adult Fasciola hepatica.

The dosage level of clorsulon supplied by Vetrimec™ Plus is effective only against adult liver flukes (Fasciola hepatica).

DESCRIPTION

PRODUCT DESCRIPTION: Vetrimec™ Plus is a ready-to-use sterile solution containing 1% w/v ivermectin, 10% w/v clorsulon, 40% glycerol formal, and propylene glycol, q.s. ad 100%. It is formulated to deliver the recommended dose level of 200 mcg ivermectin/kg and 2 mg clorsulon/kg given subcutaneously behind the shoulder at the rate of 1 mL per 110 lb (50 kg) body weight.

MECHANISM OF ACTION

MODE OF ACTION: Ivermectin is a member of the macrocyclic lactone class of endectocides which have a unique mode of action. Compounds of the class bind selectively and with high affnity to glutamate-gated chloride ion channels which occur in invertebrate nerve and muscle cells. This leads to an increase in the permeability of the cell membrane to chloride ions with hyperpolarization of the nerve or
muscle cell, resulting in paralysis and death of the parasite. Compounds of this class may also interact with other ligand-gated chloride channels, such as those gated by the neurotransmitter gamma-aminobutyric acid (GABA).

The margin of safety for compounds of this class is attributable to the fact that mammals do not have glutamate-gated chloride channels, the macrocyclic lactones have a low affnity for other mammalian ligand-gated chloride channels and they do not readily cross the blood-brain barrier. Clorsulon is rapidly absorbed into the circulating blood. Erythrocytes with bound drug as well as plasma are ingested by Fasciola hepatica. Adult Fasciola hepatica are killed by clorsulon because of inhibition of enzymes in the glycolytic pathway, which is their primary source of energy.

INDICATIONS AND USAGE

INDICATIONS: Vetrimec™ Plus is indicated for the effective treatment and control of the following parasites in cattle:
Gastrointestinal Roundworms (adults and fourth-stage larvae):
Ostertagia ostertagi (including inhibited O. ostertagi)

O. lyrata

Haemonchus placei

Trichostrongylus axei

T. colubriformis

Cooperia oncophora

C. punctata

C. pectinata

Bunostomum phlebotomum

Nematodirus helvetianus (adults only)

N. spathiger (adults only)

Oesophagostomum radiatum

Lungworms (adults and fourth-stage larvae):
Dictyocaulus viviparus

Liver Flukes:
Fasciola hepatica (adults only)

Cattle Grubs (parasitic stages):

Hypoderma bovis

H. lineatum

Sucking Lice:

Linognathus vituli

Haematopinus eurysternus

Solenopotes capillatus

Mange Mites (Cattle Scab*):
Psoroptes ovis (syn. P. communis var. bovis)
Sarcoptes scabiei var. bovis

Persistent Activity: Ivermectin and clorsulon injection has been proved to effectively control infections and to protect cattle from reinfection with Dictyocaulus viviparus and Oesophagostomum radiatum for 28 days after treatment; Ostertagia ostertagi, Trichostrongylus axei and Cooperia punctata for 21 days after treatment; Haemonchus placei and Cooperia oncophora for 14 days after treatment.

*Ivermectin has been approved as a scabicide by USDA/APHIS. Federal regulations require that cattle infested with or exposed to scabies (i.e., infestations with Psoroptes ovis) be treated. Ivermectin when used according to label instructions meets this requirement. Treated cattle may be shipped interstate, but they must not be mixed with other cattle for 14 days following treatment. The federal regulations make no restriction on the movement of cattle not affected with or exposed to scabies. However, individual states have additional regulations to govern the interstate shipment of cattle and the regulatory veterinarian in the state of destination should be consulted for
applicable regulations on the use of ivermectin in the control of scabies.

DOSAGE AND ADMINISTRATION

DOSAGE:Vetrimec™ Plus should be given only by subcutaneous injection at a dose volume of 1 mL per 110 lb. (50 kg) body weight. This volume will deliver 10 mg ivermectin and 100 mg clorsulon. For example:

Body Weight (lb) | Dose Volume (mL)
220 | 2
330 | 3
440 | 4
550 | 5
660 | 6
770 | 7
880 | 8
990 | 9
1100 | 10

ADMINISTRATION: Vetrimec™ Plus (ivermectin and clorsulon) is to be given subcutaneously only. Animals should be appropriately restrained to achieve the proper route of administration. Use of a 16-gauge, ½” to ¾” sterile needle is recommended. Inject the solution subcutaneously (under the skin) behind the shoulder (see illustration).

When using the 500 mL or 1000 mL package size, use only automatic syringe equipment.

Use sterile equipment and sanitize the injection site by applying a suitable disinfectant. Clean, properly disinfected needles should be used to reduce the potential for injection site infections.

No special handling or protective clothing is necessary.

The viscosity of the product increases in cool temperatures. Andministering Vetrimec™ Plus at temperatures of 5°C (41°F) or below may be difficult. Users can make dosing easier by warming both the product and the injection equipment to about 15°C (59°F).

Use within 28 days of first puncture and puncture a maximum of 14 times with a dosage delivery device.

ANIMAL SAFETY: In breeding animals (bulls and cows), ivermectin and clorsulon used at the recommended level had no effect on breeding performance.

WARNING: NOT FOR USE IN HUMANS.
Keep this and all drugs out of reach of children.
The Safety Data Sheet (SDS) contains more detailed occupational safety information. To report adverse effects, obtain an SDS or for assistance, contact Bimeda, Inc. at 1-888-524-6332.

RESIDUE WARNING: Do not treat cattle within 21 days of slaughter. Because a withdrawal period in milk has not been established, do not use in female dairy cattle of breeding age. A withdrawal period has not been established for this product in pre-ruminating calves. Do not use in calves to be processed for veal.

PRECAUTIONS

PRECAUTIONS: Transitory discomfort has been observed in some cattle following subcutaneous administration. Soft tissue swelling at the injection site has also been observed. These reactions have disappeared without treatment. Divide doses greater than 10 mL between two injection sites to reduce occasional discomfort or site reaction. Different injection sites should be used for other parenteral products.

Vetrimec™ Plus has been developed specifcally for use in cattle only. This product should not be used in other animal species as severe adverse reactions, including fatalities in dogs, may result.

For subcutaneous injection in cattle only.

This product is not for intravenous or intramuscular use.

Restricted Drug (California) - Use Only as Directed.

When to Treat Cattle with Grubs: Vetrimec™ Plus effectively controls all stages of cattle grubs. However, proper timing of treatment is important. For most effective results, cattle should be treated as soon as possible after the end of the heel fy (warble fy) season.

Destruction of Hypoderma larvae (cattle grubs) at the period when these grubs are in vital areas may cause undesirable host-parasite reactions including the possibility of fatalities. Killing Hypoderma lineatum when it is in the tissue surrounding the esophagus (gullet) may cause bloat; killing H. bovis when it is in the vertebral canal may cause staggering or paralysis. These reactions are not specifc to treatment with Vetrimec™ Plus, but can occur with any successful treatment of grubs. Cattle should be treated either before or after stages of grub development. Consult your veterinarian concerning the proper time for treatment.

Cattle treated with Vetrimec™ Plus after the end of the heel fly season may be retreated with ivermectin during the winter for internal parasites, mange mites, or sucking lice, without danger of grub-related reactions. A planned parasite control program is recommended.

Protect product from light.

Environmental Safety: Studies indicate that when ivermectin comes in contact with soil, it readily and tightly binds to the soil and becomes inactive over time. Free ivermectin may adversely affect fish and certain aquatic organisms. Do not permit water runoff from feedlots to enter lakes,streams or ponds. Do not contaminate water by direct application or by improper disposal of drug containers. Dispose of containers in an approved landfill or by incineration.

As with other avermectins, ivermectin is excreted in the dung of treated animals and can inhibit the reproduction and growth of pest and beneficial insects that use dung as a source of food and for reproduction. The magnitude and duration of such effects are species and life-cycle specific. When used according to label directions, the product is not expected to have an adverse impact on populations of dung-dependent insects.

HOW SUPPLIED

HOW SUPPLIED: Vetrimec™ Plus is available in two ready-to-use sizes:

The 500 mL plastic bottle is suitable for use with automatic syringe equipment. Each bottle contains suffcient solution to treat 100 head of 550 lb (250 kg) cattle.

The 1000 mL plastic bottle is suitable for use with automatic syringe equipment. Each bottle contains suffcient solution to treat 200 head of 550 lb (250 kg) cattle.

STORAGE AND HANDLING

Store at 20ºC to 25ºC (68°F to 77°F). Protect from light.